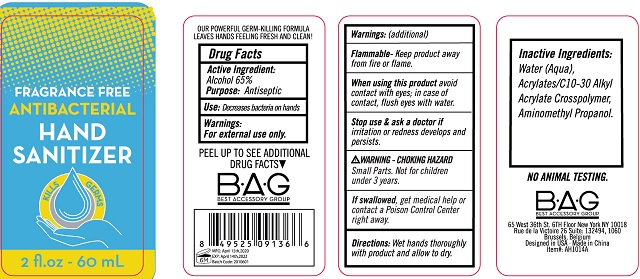 DRUG LABEL: Fragrance Free Antibacterial Hand Sanitizer
NDC: 56136-306 | Form: GEL
Manufacturer: Ganzhou Olivee Cosmetic Co., Ltd.
Category: otc | Type: HUMAN OTC DRUG LABEL
Date: 20200416

ACTIVE INGREDIENTS: ALCOHOL 65 mL/100 mL
INACTIVE INGREDIENTS: WATER; CARBOMER INTERPOLYMER TYPE A (ALLYL SUCROSE CROSSLINKED); AMINOMETHYLPROPANOL; CARBOMER COPOLYMER TYPE A

HAND SANITIZER

Active Ingredient

Alcohol 65%

Purpose

Antiseptic

Use

Decrease bacteria on hands.

Warnings

For external use only.

Flammable. Keep product away from fire or flame.

When using this product

avoid contact with eyes; in case of contact, flush eyes with water.

Stop use and ask a doctor if

irritation or redness develops and persists.

Keep out of reach of children.

If swallowed, get medical help or contact a Poison Control Center right away.

Small Parts. Not for children under 3 years.

Directions

Wet hands thoroughly with product and allow to dry.

Inactive ingredients

Water (Aqua), Acrylates/C10-30 Alkyl Acrylate Crosspolymer, Aminomethyl Propanol